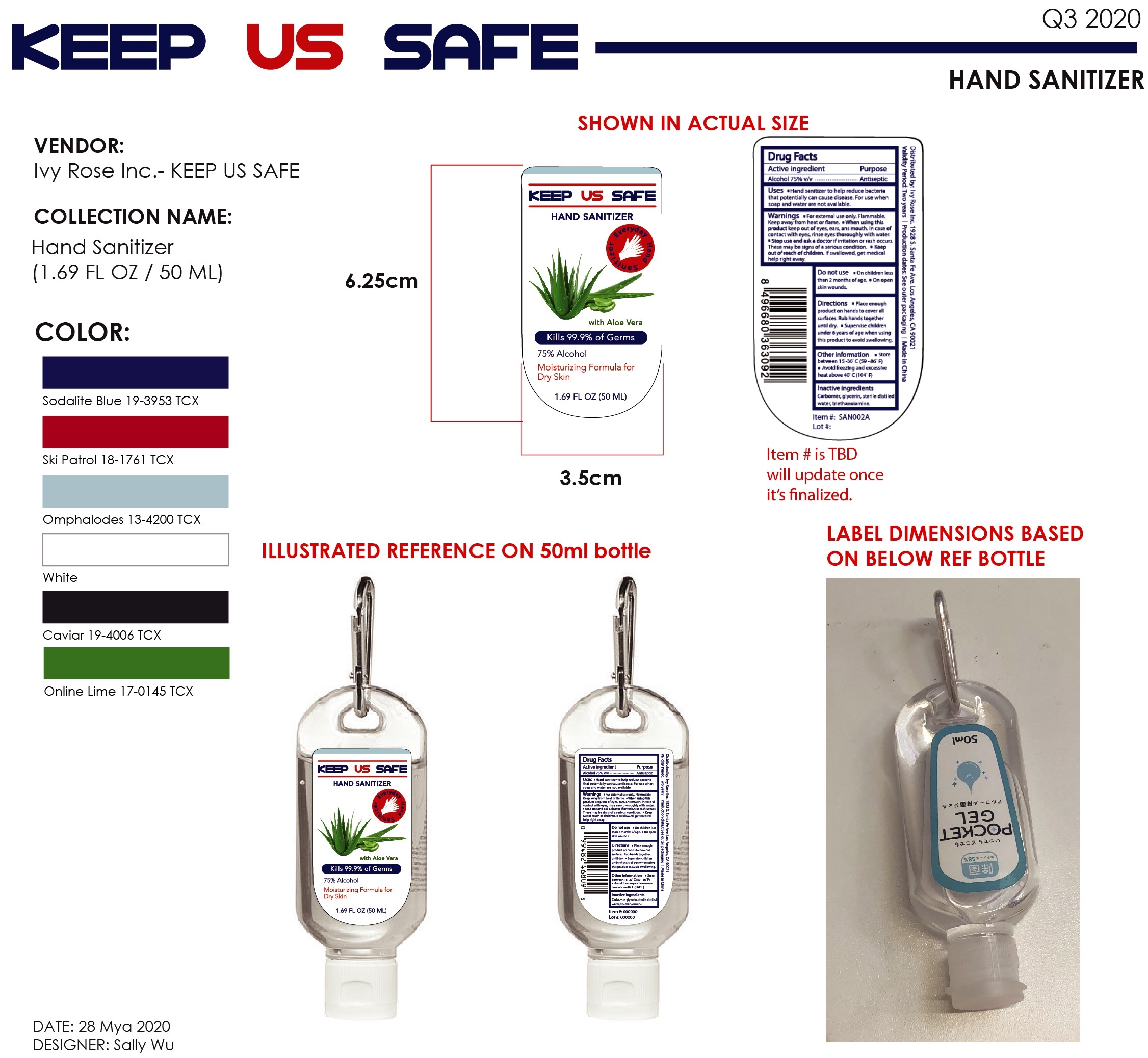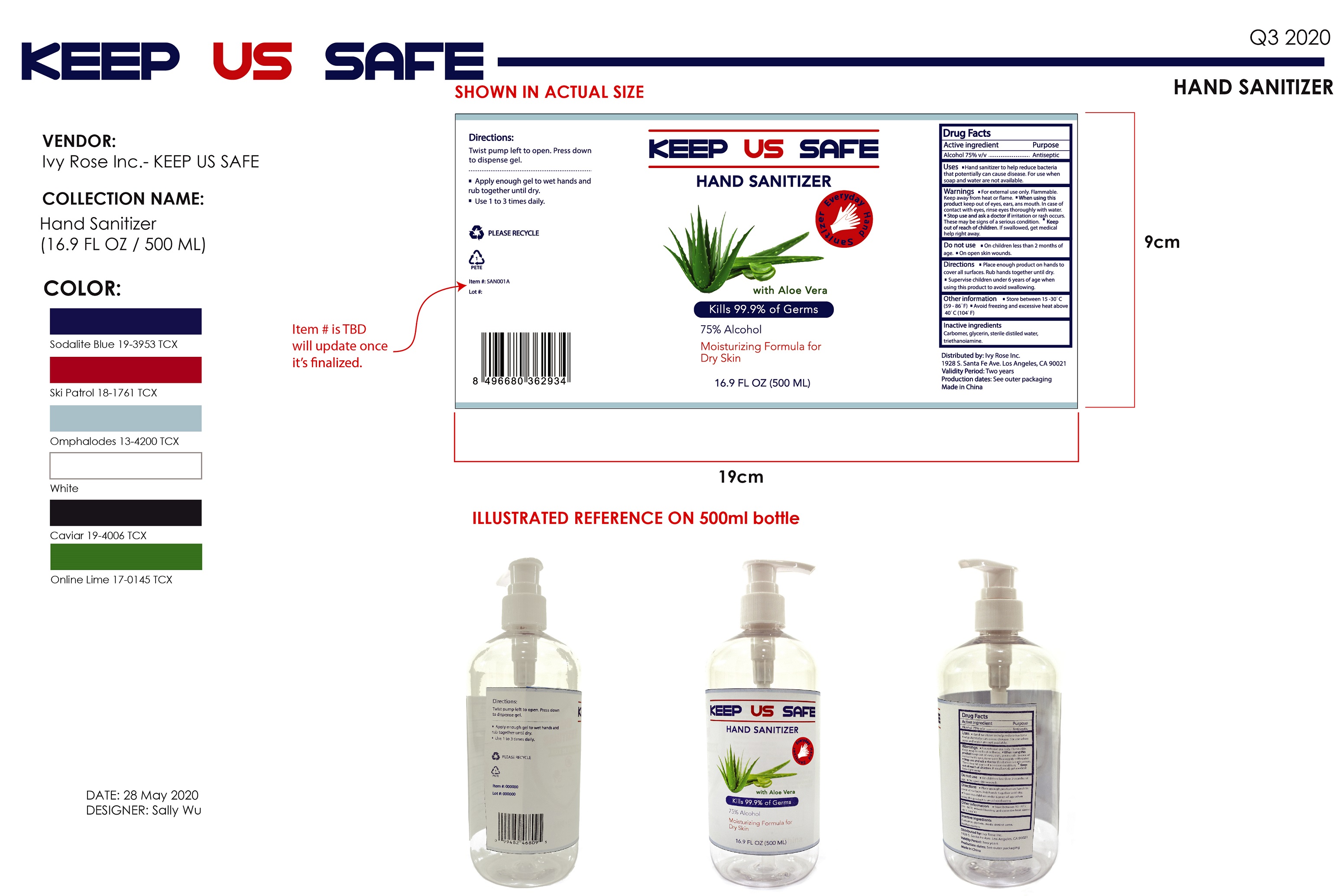 DRUG LABEL: KEEP US SAFE HAND SANITIZER
NDC: 79247-000 | Form: GEL
Manufacturer: Ivy Rose Inc
Category: otc | Type: HUMAN OTC DRUG LABEL
Date: 20200710

ACTIVE INGREDIENTS: ALCOHOL 0.75 mL/1 mL
INACTIVE INGREDIENTS: CARBOMER HOMOPOLYMER, UNSPECIFIED TYPE; GLYCERIN; WATER; TROLAMINE

KEEP US SAFE HAND SANITIZER

Active ingredient

Alcohol 75% v/v

Purpose

Antiseptic

Uses

- Hand sanitizer to help reduce bacteria that potentially can cause disease. For use when soap and water are not available.

Warnings

For external use only. Flammable. Keep away from heat or flame.

When using this product

- keep out of eyes, ears, ans mouth. In case of contact with eyes, rinse eyes thoroughly with water.

Stop use and ask a doctor

- if irritation or rash occurs. These may be signs of a serious condition.

Keep out of reach of children.

- If swallowed, get medical help right away.

Do not use

- On children less than 2 months of age.
- On open skin wounds.

Directions

- Place enough product on hands to cover all surfaces. Rub hands together until dry.
- Supervise children under 6 years of age when using this product to avoid swallowing.

Other information

- store between 15-30° C (59-86° F)
- Avoid freezing and excessive heat above 40° C (104° F)

Inactive ingredients

Carbomer, glycerin, sterile distilled water, triethanolamine.